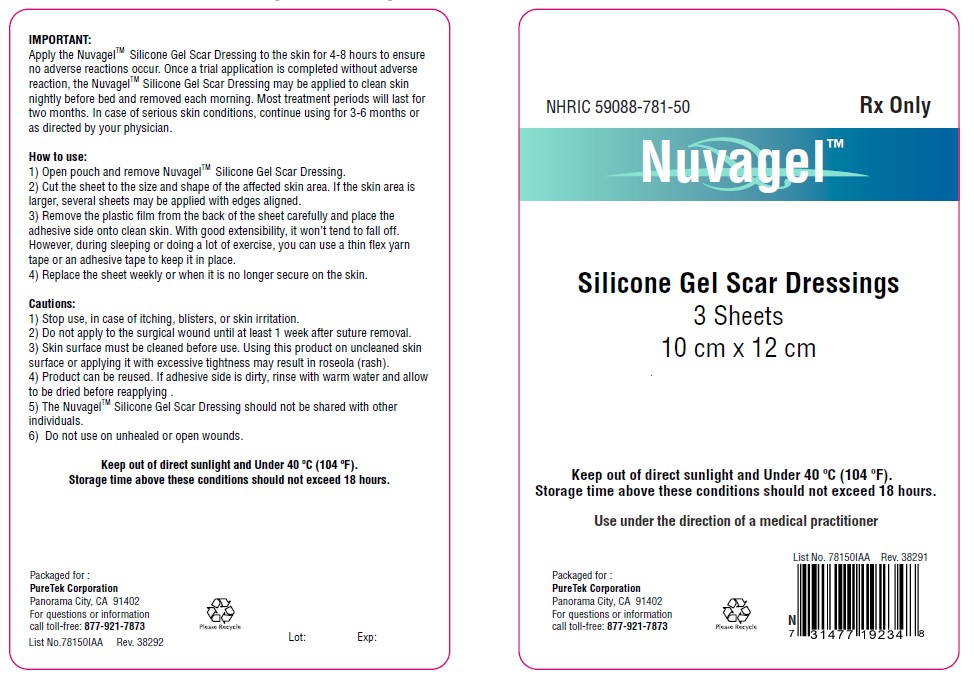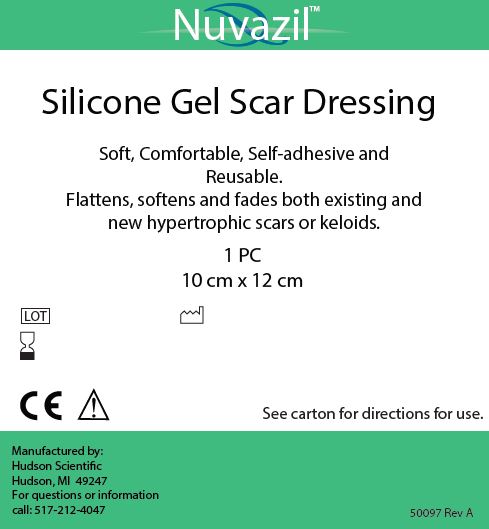 DRUG LABEL: Nuvagel
NDC: 59088-781
Manufacturer: PureTek Corporation
Category: other | Type: MEDICAL DEVICE
Date: 20210409

Nuvagel™

Rx Only

For external use only

Description

Nuvagel™ is a Silicone Gel Scar Dressing which is soft, comfortable, self-adhesive and Reusable.

Nuvagel™ flattens, softens and fades both existing and new hypertrophic scars or keloids.

Indications and Usage

For non-invasive management of both existing and new hypertrophic scars or keloids.

Use under the direction of a medical practitioner.

Contraindications:

Nuvagel™ is contraindicated for patients with sensitivity to silicone.

Warnings and Precautions:

For external use only.

1) Stop use, in case of itching, blisters, or skin irritation.
2) Do not apply to the surgical wound until at least 1 week after suture removal.
3) Skin surface must be cleaned before use. Using this product on uncleaned skin
surface or applying it with excessive tightness may result in roseola (rash).
4) Product can be reused. If adhesive side is dirty, rinse with warm water and allow
to be dried before reapplying .
5) The NuvagelTM Silicone Gel Scar Dressing should not be shared with other
individuals.
6) Do not use on unhealed or open wounds.

Keep out of direct sunlight and Under 40°C (104 °F).

Storage time above these conditions should not exceed 18 hours.

Dosage & Administration:

Important:
Apply the Nuvagel™ Silicone Gel Scar Dressing to the skin for 4-8 hours to ensure no adverse reactions occur. Once a trial application is completed without adverse reaction, the Nuvagel™ Silicone Gel Scar Dressing may be applied to clean skin nightly before bed and removed each morning. Most treatment period will last for two months. In case of serious skin conditions, continue using for 3-6 months or as directed by your physician.

How to use:

1. Open pouch and remove Nuvagel™ Silicone Gel Scar Dressing.
2. Cut the sheet to the size and shape of the affected skin area. If the skin area is larger, several sheets may be applied with edges aligned.
3. Remove the plastic film from the back of the sheet carefully and place the adhesive side onto clean skin. With good extensibility, it won’t tend to fall off. However, during sleeping or doing a lot of exercise, you can use a thin flex yarn tape or an adhesive tape to keep it in place.
4. Replace the sheet weekly or when it is no longer secure on the skin.

How Supplied:

Nuvagel™ is provided in a shipping pouch containing three (3) individually wrapped pouches. Each pouch contains one Nuvagel™ 10 cm x 12 cm pad.

Storage and Handling:

Keep out of direct sunlight and under 40°C (104°F).

Storage time above these conditions should not exceed 18 hours.

Adverse Reactions:

In rare circumstances, use of Nuvagel™ may cause skin irritations including redness, stinging or other irritations. Those effects should go away after use of Nuvagel™ is discontinued.

Manufacturer:

Nuvagel™ is manufactured by:

Hudson Scientific LLC
103 W. Main St.
Hudson, MI 49247

Rx Only

Nuvazil™ Pouch Label

The label on each pouch containing a Nuvazil™ sheet is pictured below:

Nuvagel™

Packaged for :

PureTek Corporation
Panorama City, CA 91402
For questions or information
call toll-free: 877-921-7873